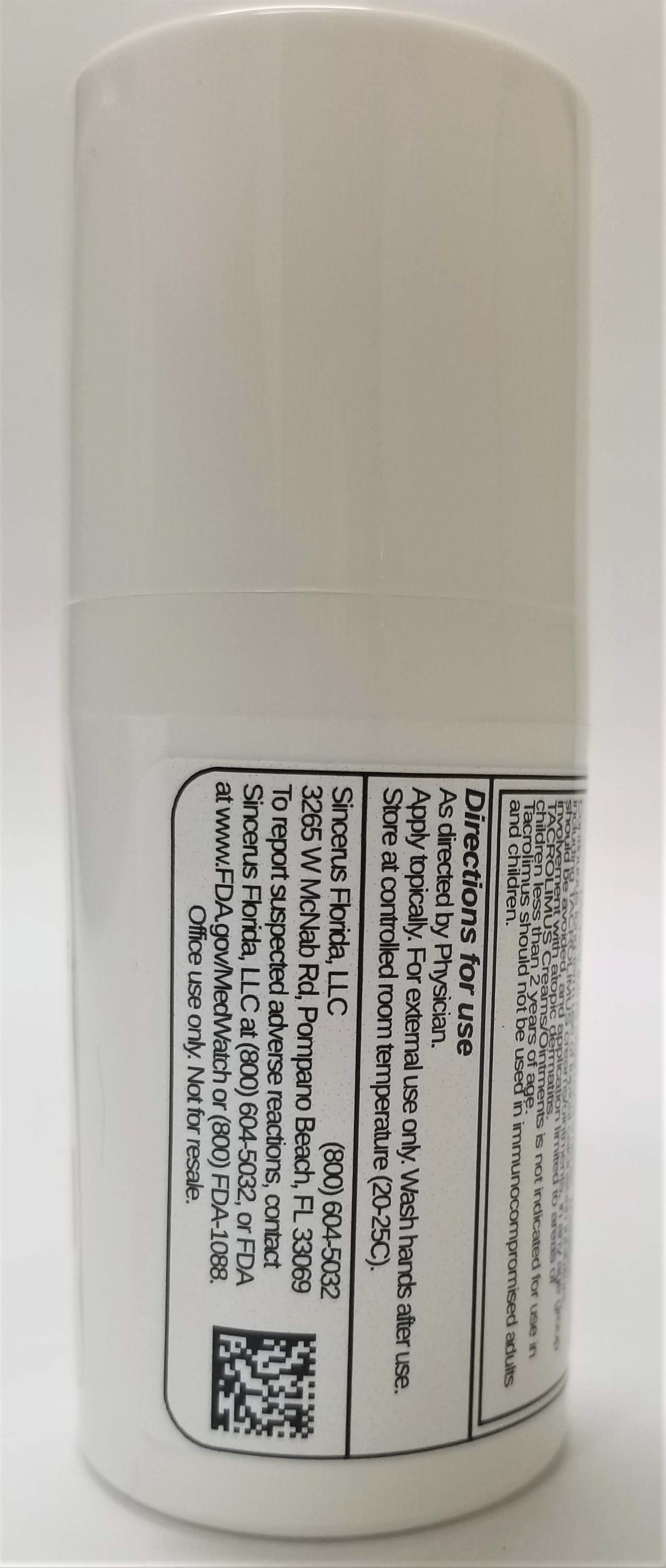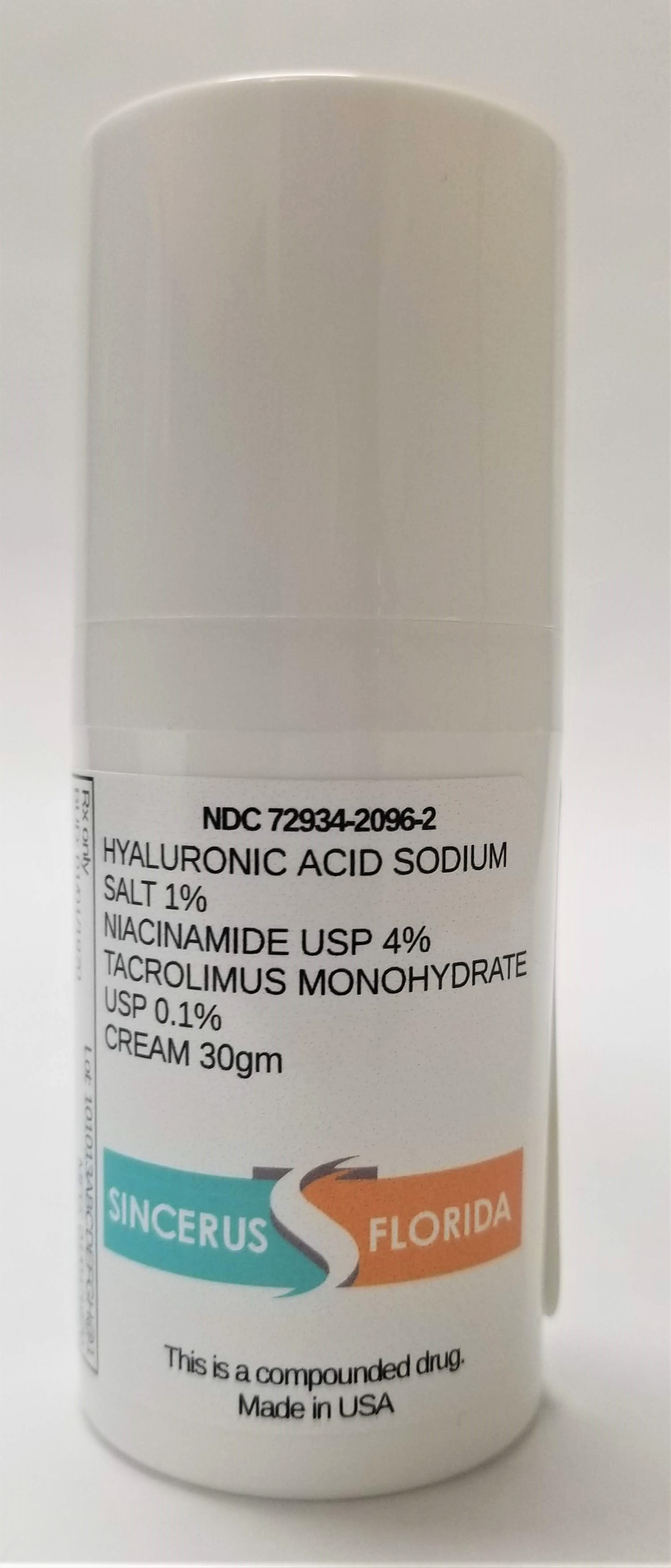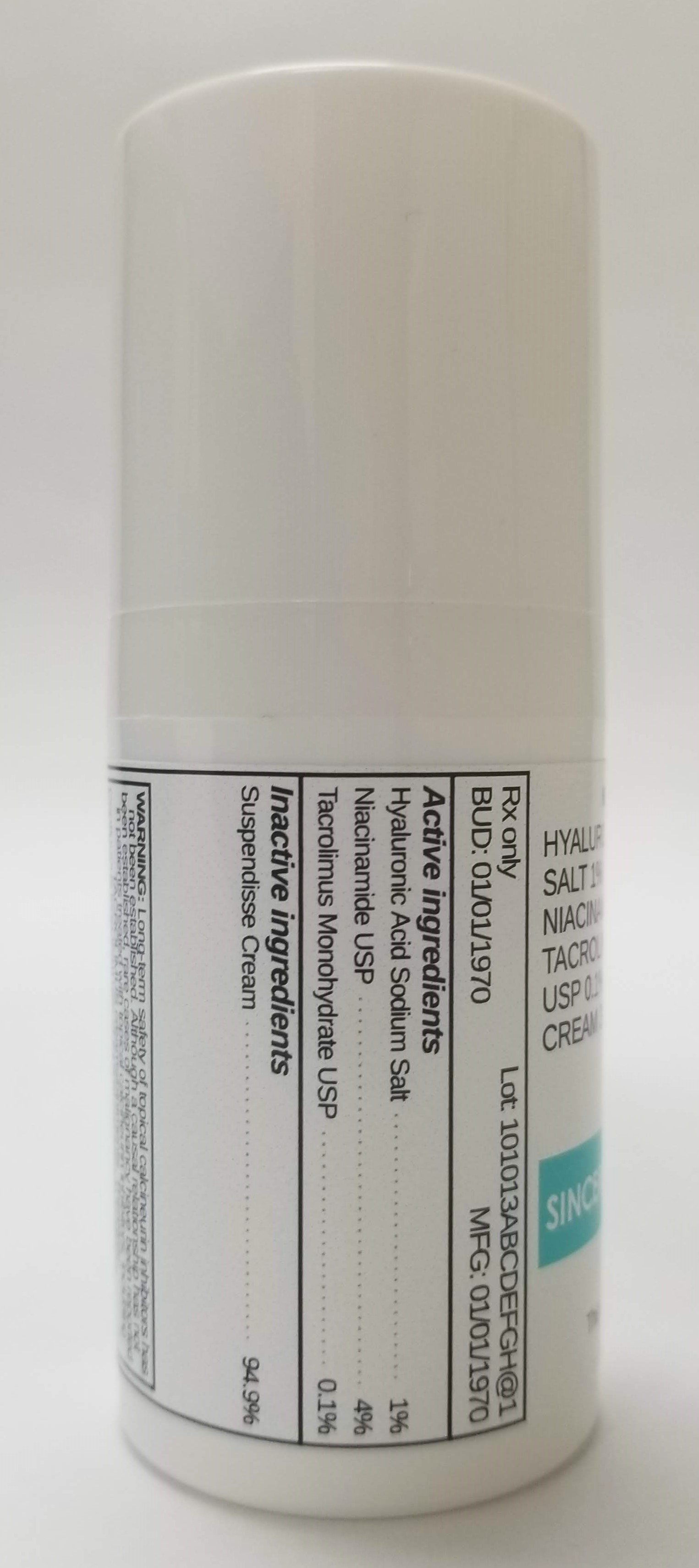 DRUG LABEL: HYALURONIC ACID SODIUM SALT 1% / NIACINAMIDE 4% / TACROLIMUS 0.1%
NDC: 72934-2096 | Form: CREAM
Manufacturer: Sinceru Florida, LLC
Category: prescription | Type: HUMAN PRESCRIPTION DRUG LABEL
Date: 20190424

ACTIVE INGREDIENTS: TACROLIMUS 0.1 g/100 g; NIACINAMIDE 4 g/100 g; HYALURONIC ACID 1 g/100 g

HYALURONIC ACID SODIUM SALT 1% / NIACINAMIDE 4% / TACROLIMUS 0.1%